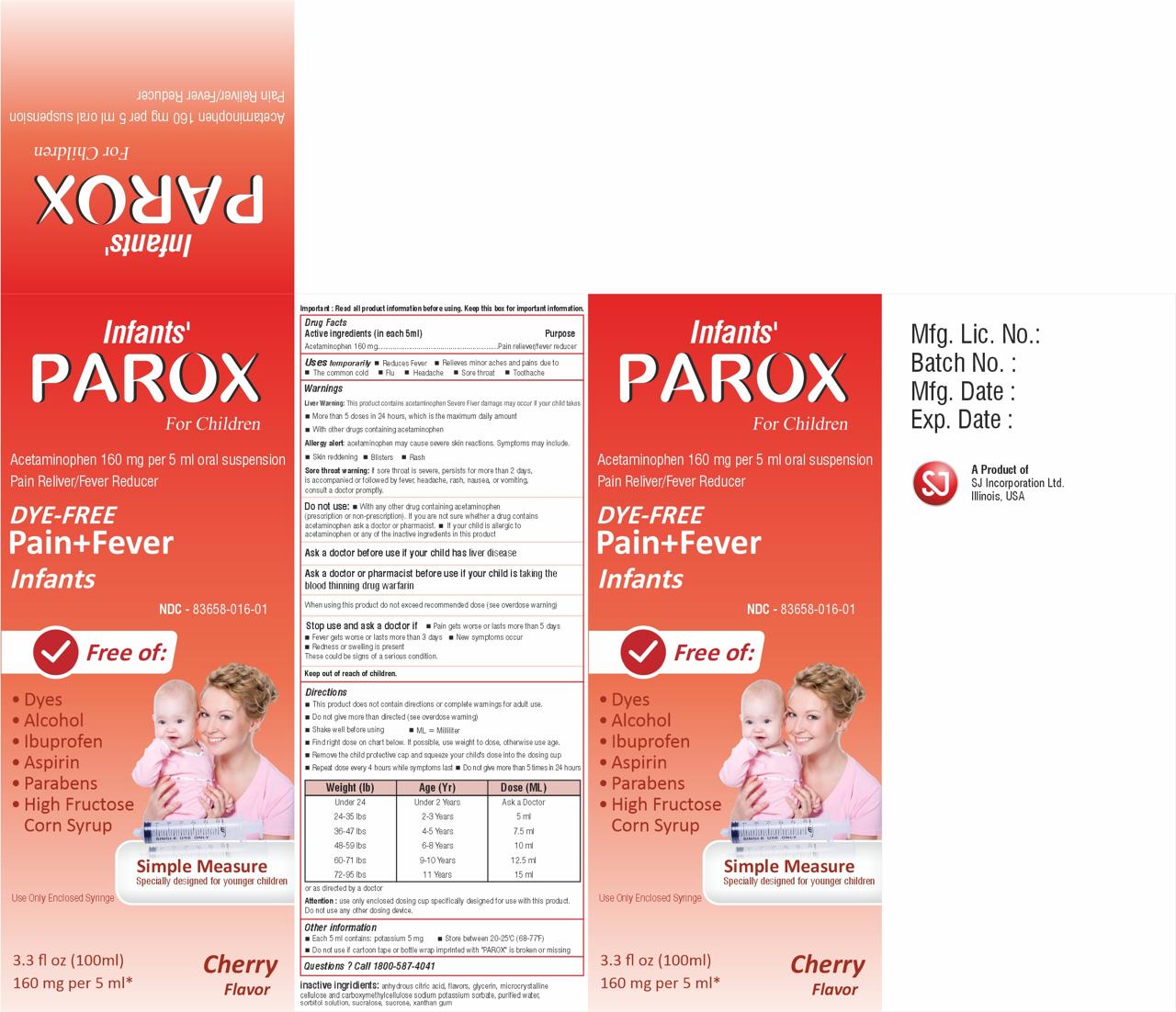 DRUG LABEL: PAROX
NDC: 83658-016 | Form: SUSPENSION
Manufacturer: SJ INCORPORATION LTD
Category: otc | Type: HUMAN OTC DRUG LABEL
Date: 20240527

ACTIVE INGREDIENTS: ACETAMINOPHEN 160 mg/5 mL
INACTIVE INGREDIENTS: ANHYDROUS CITRIC ACID; GLYCERIN; MICROCRYSTALLINE CELLULOSE; CARBOXYMETHYLCELLULOSE SODIUM (0.7 CARBOXYMETHYL SUBSTITUTION PER SACCHARIDE; 150 MPA.S AT 1%); POTASSIUM SORBATE; WATER; SORBITOL SOLUTION; SUCRALOSE; SUCROSE; XANTHAN GUM

INFAN'S PAROX FOR CHILDREN
ACETAMINOPHEN 160 MG PER 5 ML ORAL SUSPENSION
PAIN RELIEVE/FEVER REDUCER

Active Ingredient (in each 5mL)

Acetaminophen, 160mg

Inactive Ingredients

Anhydrous citric acid, cherry flavor, glycerin,microcrystalline cellulose,carboxymethylcellulose sodium, potassium sorbate, purified water, sorbitol solution, sucralose, sucrose, xanthan gum

Purpose

Pain reliever/fever reducer

Uses

Temporarily: • Reduces fever
Relieves minor aches and pains due to: • the common cold • flu • headache • sore throat • toothache

Warnings

Liver Warning: This product contains acetaminophen. Severe liver damage may occur if your child takes

- More than 5 doses in 24 hours, which is the maximum daily amount for this product
- With other drugs containing acetaminophen

Allergy alert:acetaminophen may cause severe skin reactions. Symptoms may include:

- skin reddening
- blisters
- rash.

Sore throat warning:If sore throat is severe, persists for more than 2 days, is accompanied or followed by fever, headache, rash, nausea, or vomiting consult a doctor promptly.

Do not Use:

- With any other drug containing acetaminophen(prescription or non-prescription). If you are not sure whether a drug contains acetaminophen ask a doctor or pharmacist.
- If your child is allergic to acetaminophen or any of the inactive ingredients in this product

Ask a doctor before use if your child hasliver disease

Ask a doctor or pharmacist before use ifyour child is taking the blood thinning drug warfarin.

When Using this product do not exceed recommended dose(see overdose warning)

Stop use and ask a doctor if

- pain gets worse or lasts more than 5 days
- fever gets worse or lasts more than 3 days
- new symptoms occur
- redness or swelling is present.

These could be signs of a serious condition.

Keep out of reach of children

Do not use

- with any other drug containing acetaminophen (prescription or nonprescription). If you are not sure whether a drug contains acetaminophen, ask a doctor or pharmacist
- If your child is allergic to acetaminophen or any of the inactive ingredients in this product

Directions

- This product does not contain directions or complete warnings for adult use.
- Do not give more than directed (see overdose warning)
- Shake well before using, ml= milliliter
- Find the right dose on chart below. If possible, use weight to confirm, otherwise use age
- Remove the child protective cap and squeeze your child's dose in to the dosing cup
- Repeat dose every 4 hours while symptoms last
- Do not give more than 5 times in 24 hours or as directed by a doctor

Attention: Use only enclosed dosing cup specifically designed for use with this product. Do not use any other dosing device.

Dosing Chart

Weight (lbs) | Age (Years) | Dose (mL)
under 24 lbs | under 2 years | Ask a doctor
24 -35 lbs | 2 - 3 years | 5 mL
36 - 47 lbs | 4 - 5 years | 7.5 mL
48 - 59 lbs | 6 - 8 years | 10 mL
60 - 71 lbs | 9 -10 years | 12.5 mL
72 - 95 lbs | 11 years | 15 mL

Other information

- Each 5 ml contains Potassium 5 mg
- Store between 20-25ºC (68-77ºF)
- Do not use if carton tape or bottle wrap imprinted with "PAROX" is broken or missing

Questions ?

Call +1-800-587-4041

PACKAGE LABEL.PRINCIPAL DISPLAY PANEL

INFANT'S PARXO FOR CHILDREN

ACETAMINOPHEN 160 MG PER 5 ML ORAL SUSPENSION

PAIN RELIVER/FEVER REDUCER

DYE-FREE

NDC-83658-016-01

100 ML

CHERRY FLAVOR